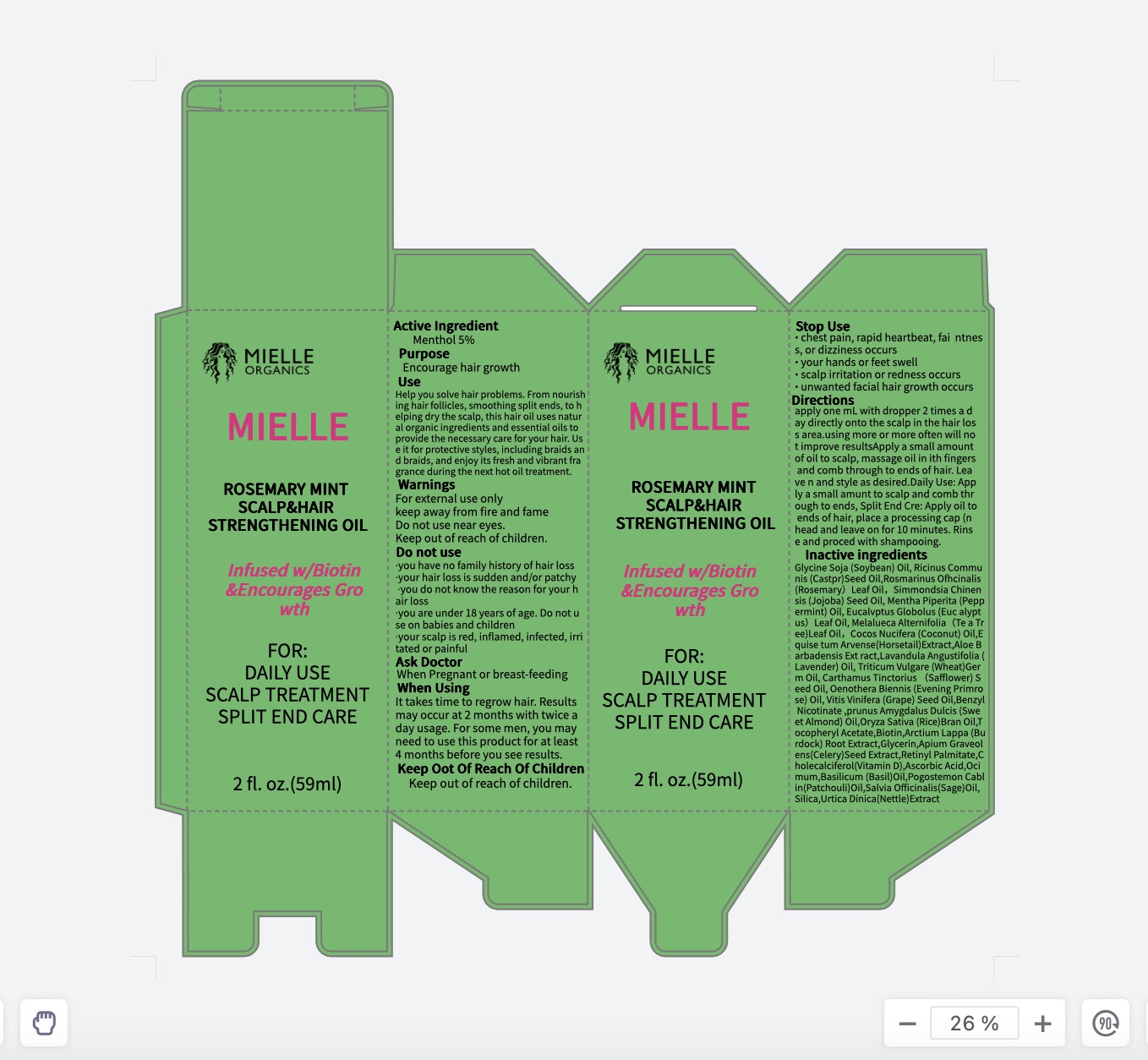 DRUG LABEL: Mielle Rosemary Mintscalp Hair Strengthening Oil
NDC: 83675-034 | Form: OIL
Manufacturer: Guangzhou Hanhai Trading Co., Ltd
Category: otc | Type: HUMAN OTC DRUG LABEL
Date: 20240204

ACTIVE INGREDIENTS: MENTHOL 5 g/100 mL
INACTIVE INGREDIENTS: SOYBEAN OIL; CASTOR OIL; COCONUT OIL; EQUISETUM ARVENSE TOP; POGOSTEMON CABLIN LEAF OIL; SILICON DIOXIDE; RICE BRAN OIL; GLYCERIN; OCIMUM GRATISSIMUM LEAF OIL; VITAMIN A PALMITATE; ASCORBIC ACID; 1-CHLORONAPHTHALENE; URTICA DIOICA LEAF; ALMOND OIL; .ALPHA.-TOCOPHEROL ACETATE; BIOTIN; ARCTIUM LAPPA ROOT OIL; SAFFLOWER OIL; ISOTACHYSTEROL 3; ALOE VERA FLOWER; SAGE OIL; ROSEMARY OIL; MENTHA PIPERITA LEAF; JOJOBA OIL; EUCALYPTUS GLOBULUS LEAF; TEA TREE OIL; LAVENDER OIL; WHEAT GERM OIL; EVENING PRIMROSE OIL; GRAPE SEED OIL; BENZYL NICOTINATE; CELERY SEED

83675-034

Active Ingredient

Menthol 5%

Purpose

Encourage hair growth

Use

Help you solve hair problems. From nourishing hair follicles, smoothing split ends, to helping dry the scalp, this hair oil uses natural organic ingredients and essential oils to provide the necessary care for your hair. Use it for protective styles, including braids and braids, and enjoy its fresh and vibrant fragrance during the next hot oil treatment.

Warnings

For external use only
keep away from fire and fame
Do not use near eyes.
Keep out of reach of children.

Do not use

• you have no family history of hair loss
• your hair loss is sudden and/or patchy
• you do not know the reason for your hair loss
• you are under 18 years of age. Do not use on babies and children
• your scalp is red, inflamed, infected, irritated or painful
• you use other medicines on the scalp

When Using

it takes time to regrow hair. Results may occur at 2 months with twice a day usage. For some men, you may need to use this product for at least 4 months before you see results.

Stop Use

• chest pain, rapid heartbeat, faintness, or dizziness occurs
• sudden, unexplained weight gain occurs
• your hands or feet swell
• scalp irritation or redness occurs
• unwanted facial hair growth occurs

Ask Doctor

When Pregnant or breast-feeding

Keep Oot Of Reach Of Children

Keep out of reach of children.

Directions

apply one mL with dropper 2 times a day directly onto the scalp in the hair loss area.
using more or more often will not improve resultsApply a small amount of oil to scalp, massage oil in ith fingers and comb through to ends of hair. Leave n and style as desired.Daily Use: Apply a small amunt to scalp and comb through to ends, Split End Cre: Apply oil to ends of hair, place a processing cap (n head and leave on for 10 minutes. Rinse and proced with shampooing.

Inactive ingredients

Glycine Soja (Soybean) Oil, Ricinus Communis (Castpr)Seed Oil,Rosmarinus Ofhcinalis (Rosemary）Leaf Oil，Simmondsia Chinensis (Jojoba) Seed Oil, Mentha Piperita (Peppermint) Oil, Eucalvptus Globolus (Euc alyptus）Leaf Oil, Menthol, Melalueca Alternifolia（Te a Tree)Leaf Oil，Cocos Nucifera (Coconut) Oil,Equise tum Arvense(Horsetail)Extract,Aloe Barbadensis Ext ract,Lavandula Angustifolia (Lavender) Oil, Triticum Vulgare (Wheat)Germ Oil, Carthamus Tinctorius （Safflower) Seed Oil, Oenothera Biennis (Evening Primrose) Oil, Vitis Vinifera (Grape) Seed